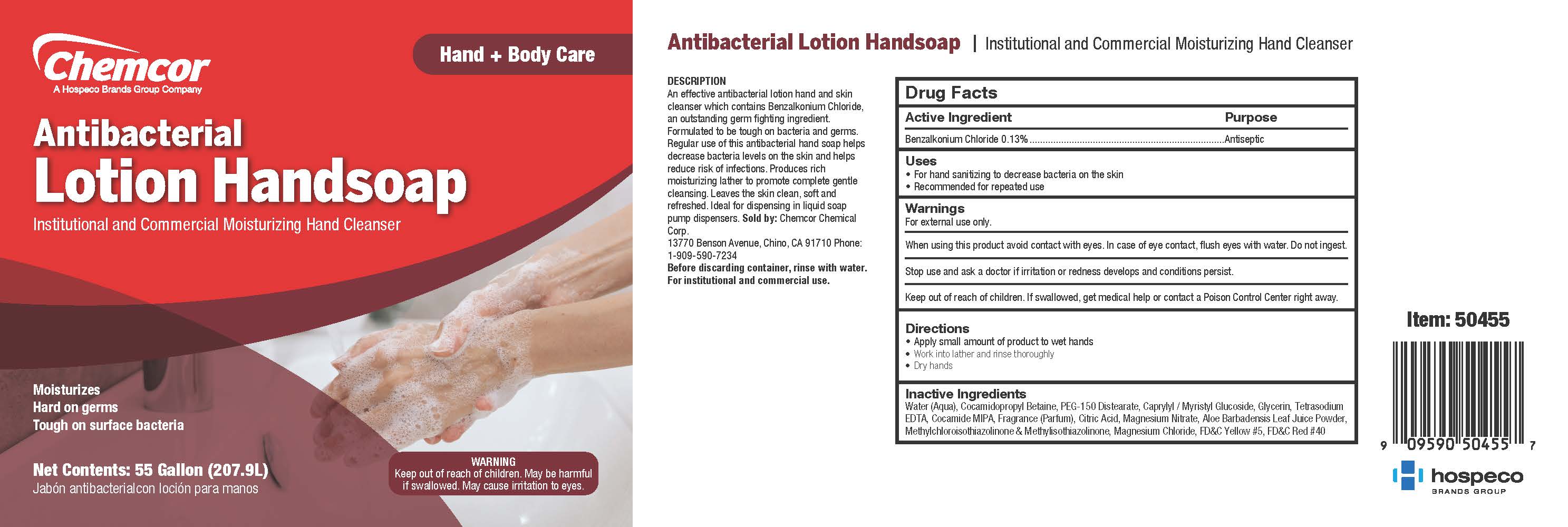 DRUG LABEL: Antibacterial Handsoap
NDC: 68041-604 | Form: LIQUID
Manufacturer: Chemcor Chemical Corporation
Category: otc | Type: HUMAN OTC DRUG LABEL
Date: 20251222

ACTIVE INGREDIENTS: BENZALKONIUM CHLORIDE .13 g/.1 L
INACTIVE INGREDIENTS: ALOE VERA LEAF; CAPRYLYL/CAPRYL OLIGOGLUCOSIDE; ANHYDROUS CITRIC ACID; COCO MONOISOPROPANOLAMIDE; COCAMIDOPROPYL BETAINE; GLYCERIN; LAURYL GLUCOSIDE; MAGNESIUM NITRATE; MALTODEXTRIN; METHYLCHLOROISOTHIAZOLINONE; METHYLISOTHIAZOLINONE; PEG-150 DISTEARATE; FD&C RED NO. 40; EDETATE SODIUM; WATER; FD&C YELLOW NO. 5

Chemcor Antibacterial Lotion Handsoap

Active Ingredient

Benzalkonium .13%

Purpose

Antimicrobial

Uses

• Handwash to help decrease bacteria on skin

• Recommended for repeated use

Warnings

For external use only.

When using this product avoid contact with eyes. In case of eye contact, flush eyes with water.

Stop use and ask a doctor if irritation or redness develops, or if condition persists.

Keep out of reach of children. If swallowed, get medical help or contact a Poison Control Center right away.

Directions

• Wet hands

• Apply product and thoroughly cover all surfaces of both hands with lather

• Rinse both hands well

• Dry hands completely

Inactive Ingredients

Aloe Barbadensis Leaf Juice, Caprylyl/Capryl Glucoside, Citric Acid, Cocamide MIPA, Cocamidopropyl Betaine, Fragrance, Glycerin, Lauryl Polyglucose, Magnesium Nitrate, Maltodextrin, Methylchloroisothiazolinone, Methylisothiazolinone, PEG 150 Distearate, FD&C Red #40, Tetrasodium EDTA, Water, FD&C Yellow #5

moisturizes

hard on germs

tough on surface bacteria

MAY BE HARMFUL IF SWALLOWED.

MAY CAUSE IRRITATION TO EYES.

SEE BACK PANEL FOR ADDITIONAL PRECAUTIONS AND FIRST AID.

institutional & commercial antibacterial hand cleanser

DESCRIPTION

AN EFFECTIVE ANTIBACTERIAL LOTION HAND AND SKIN CLEANSER WHICH CONTAINS CHLOROXYLENOL, AN OUTSTANDING GERM FIGHTING INGREDIENT. FORMULATED TO BE TOUGH ON BACTERIA AND GERMS. REGULAR USE OF THIS ANTIBACTERIAL HAND SOAP HELPS DECREASE BACTERIA LEVELS ON THE SKIN AND HELPS REDUCE RISK OF INFECTIONS. PRODUCES RICH MOISTURIZING LATHER TO PROMOTE COMPLETE GENTLE CLEANSING. LEAVES THE SKIN CLEAN, SOFT AND REFRESHED. IDEAL FOR DISPENSING IN LIQUID SOAP PUMP DISPENSERS.

Before discarding container, rinse with water.

For institutional and commercial use.